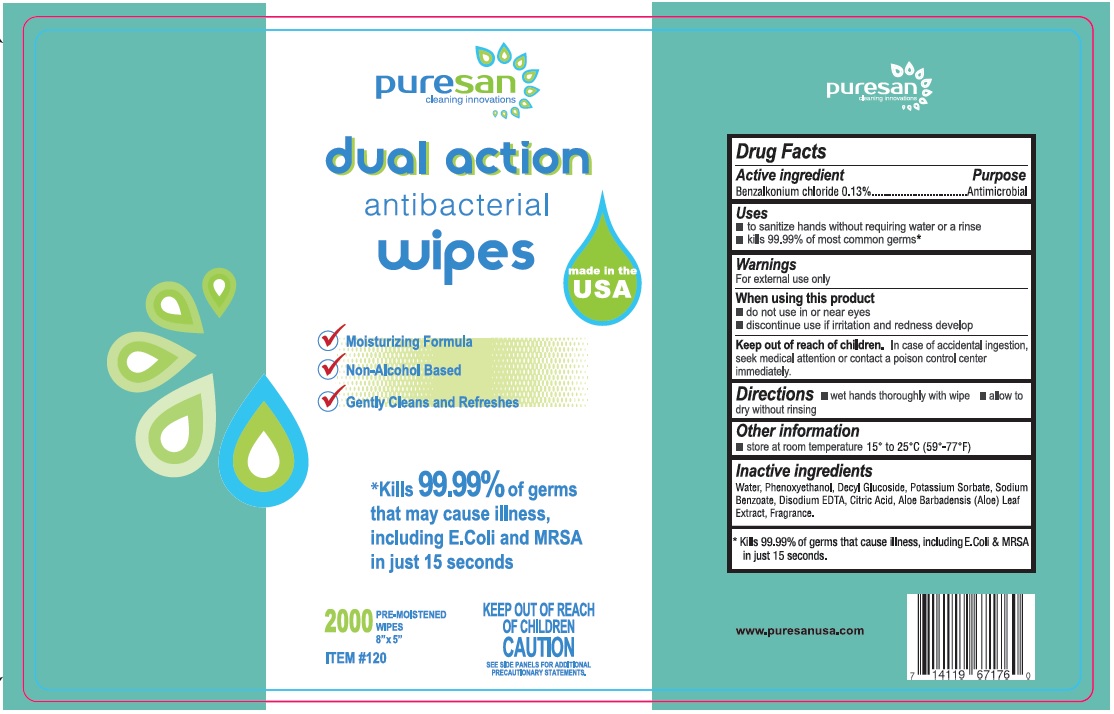 DRUG LABEL: Benzalkonium Chloride
NDC: 73062-400 | Form: CLOTH
Manufacturer: Avro Enterprises LLC
Category: otc | Type: HUMAN OTC DRUG LABEL
Date: 20251205

ACTIVE INGREDIENTS: BENZALKONIUM CHLORIDE 0.13 g/100 1
INACTIVE INGREDIENTS: DECYL GLUCOSIDE; WATER; CITRIC ACID MONOHYDRATE; ALOE VERA LEAF; PHENOXYETHANOL; EDETATE DISODIUM ANHYDROUS; POTASSIUM SORBATE; SODIUM BENZOATE

Dual Action Antibacterial Wipes

Active ingredient

Antimicrobial

Purpose

Antimicrobial

Uses

- to sanitize hands without requiring water or a rinse
- kills 99.9% of most common germs*

Warnings

For external use only

When using this product

- do not use in or near eyes
- discontinue use if irritation and redness develop

Keep out of reach of children

In case of accidental ingestion, seek medical attention or contact a posion control center immediately.

Directions

- wet hands thoroughly with wipe
- allow to dry without rinsing

Other information

store at room temperature 15° to 25° C (59° -77°F)

Inactive ingredients

Water, Phenoxyethanol, Decyl Glucoside, Potassium Sorbate, Sodium Benzoate, Disodium EDTA, Citric Acid, Aloe Barbadensis (Aloe) Leaf Extract, Fragrance

Principal Display Panel

dual action

antibacterial wipes

Moisturizing Formula

Non-Alcohol Based

Gently Cleans and Refreshes

*Kills 99.99% of germs

that may cause illness,

including E. Coli and MRSA

in just 15 seconds

2000 Pre-Moistened

Wipes

8" x 5"